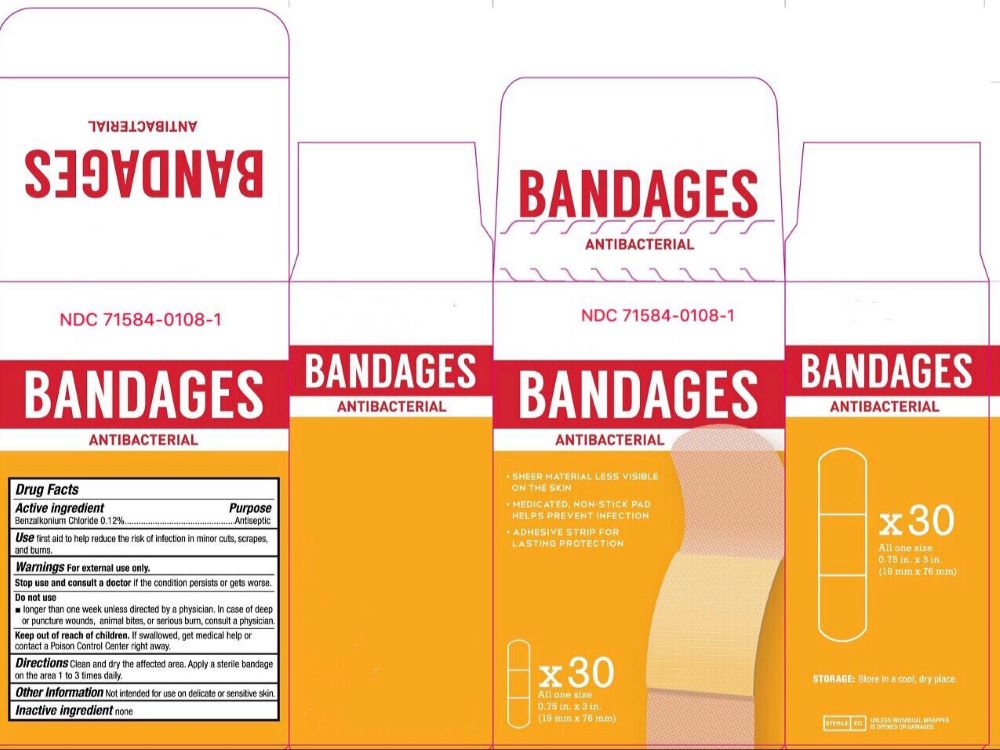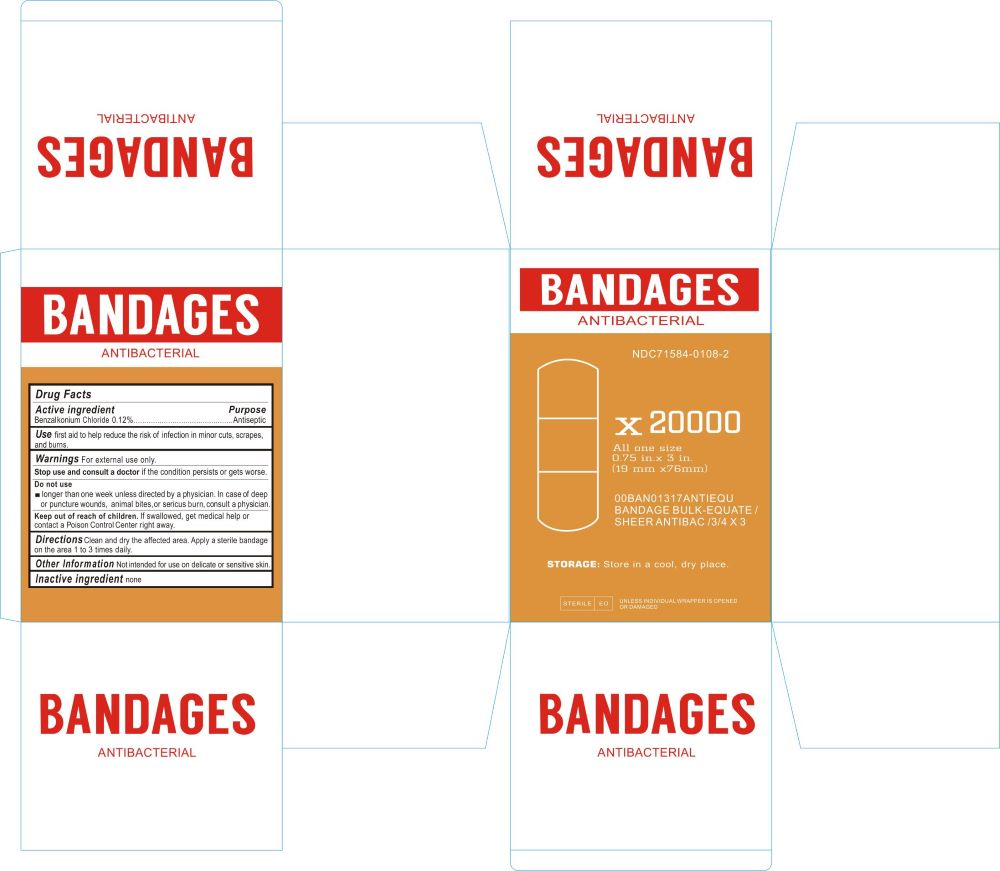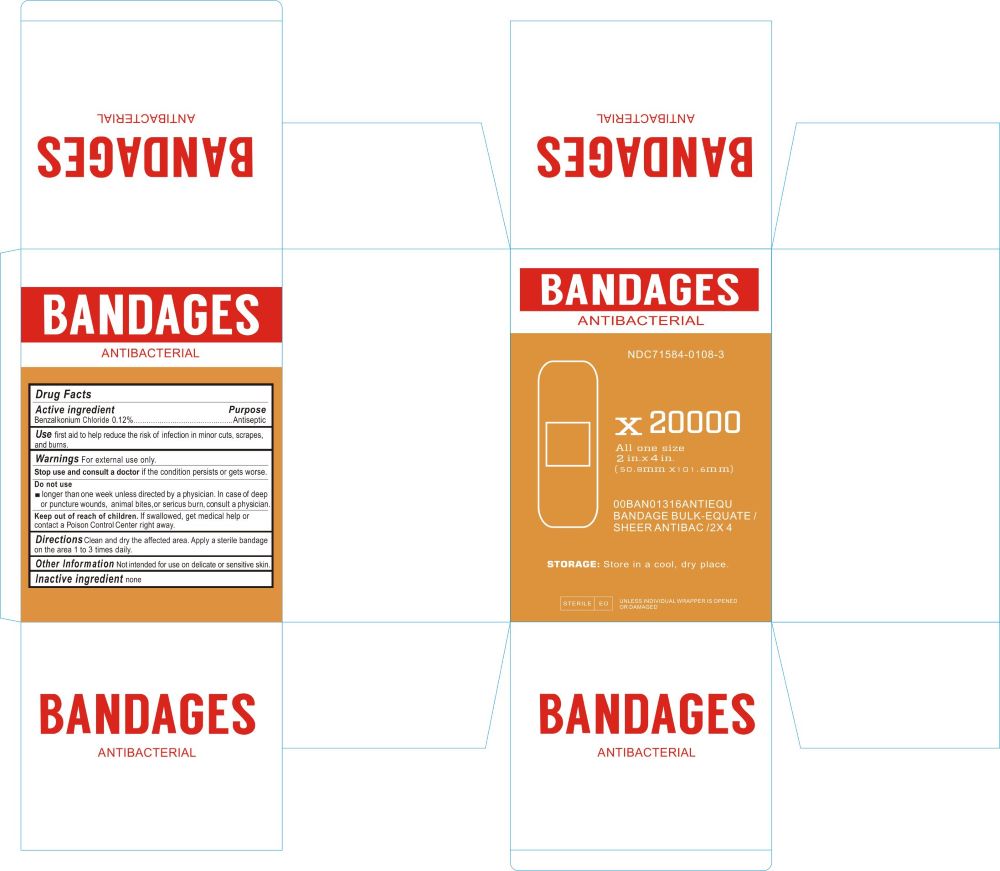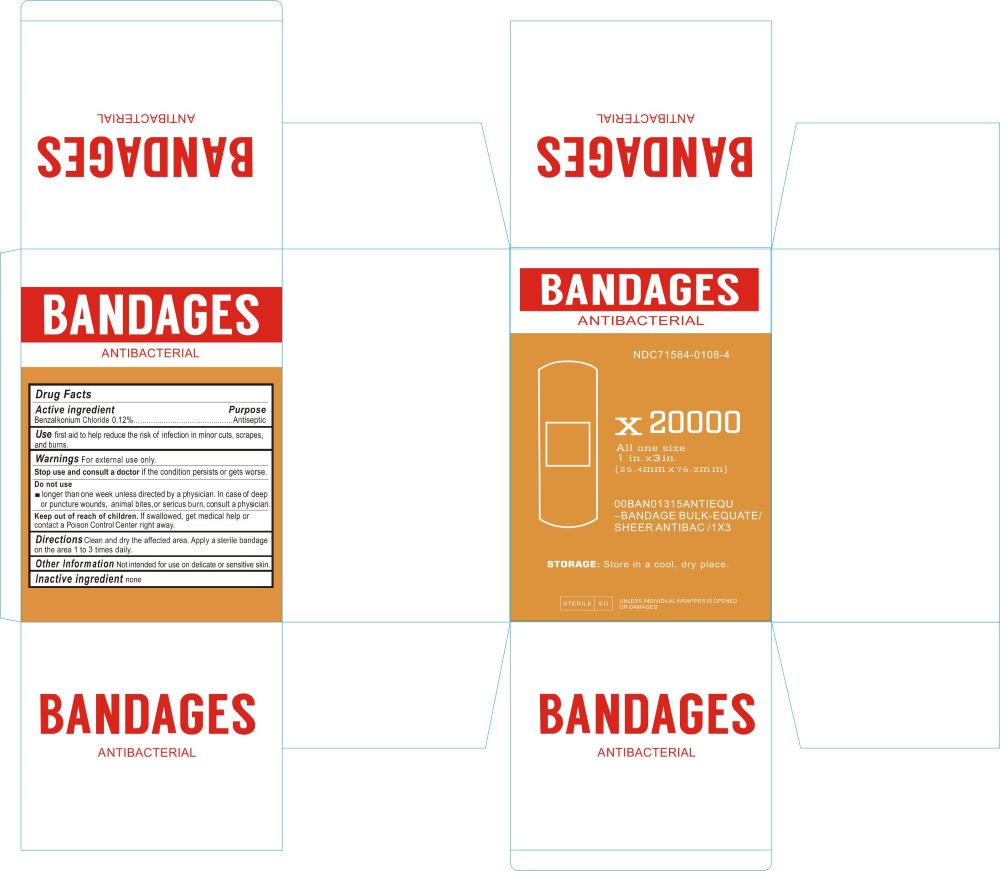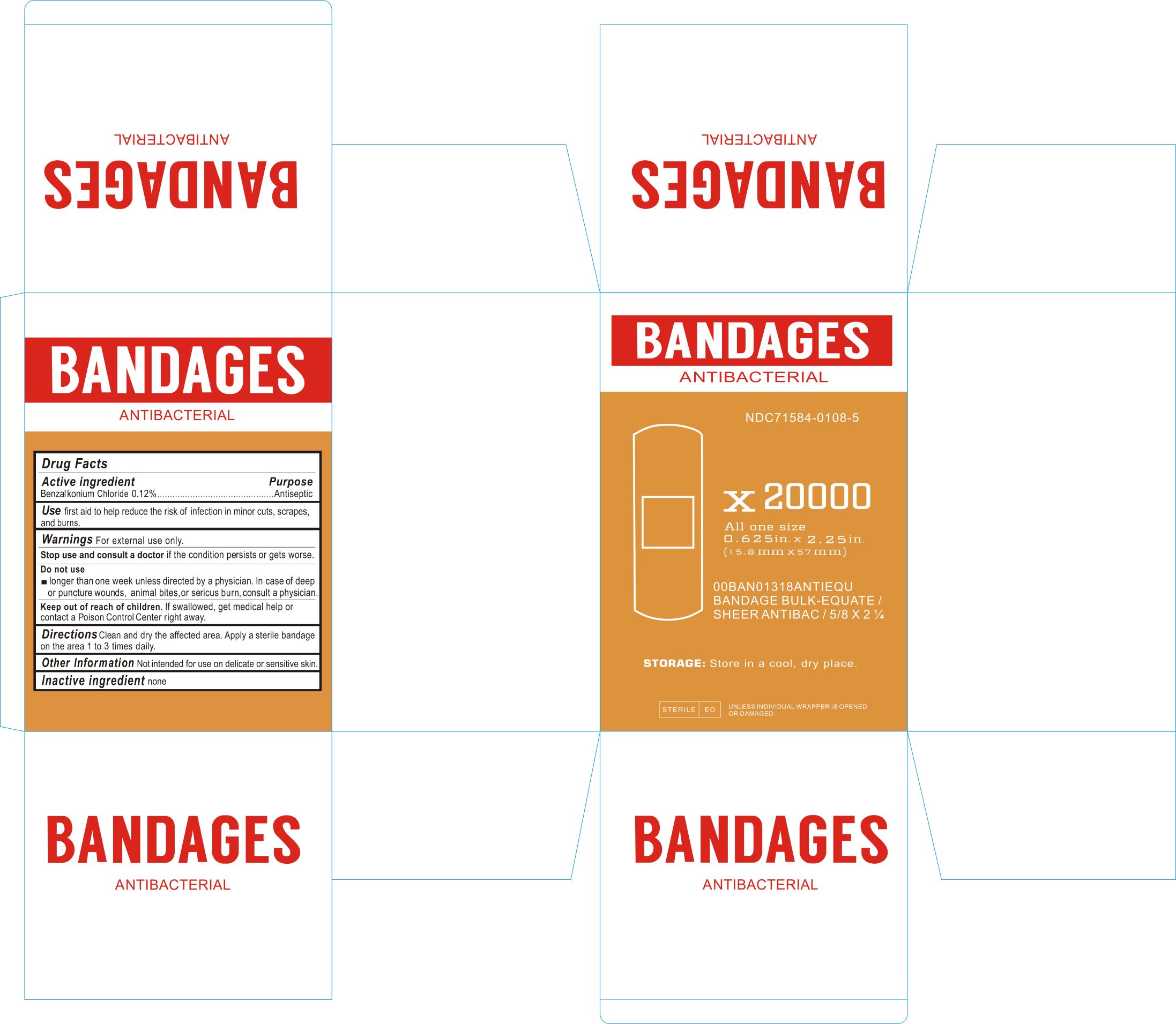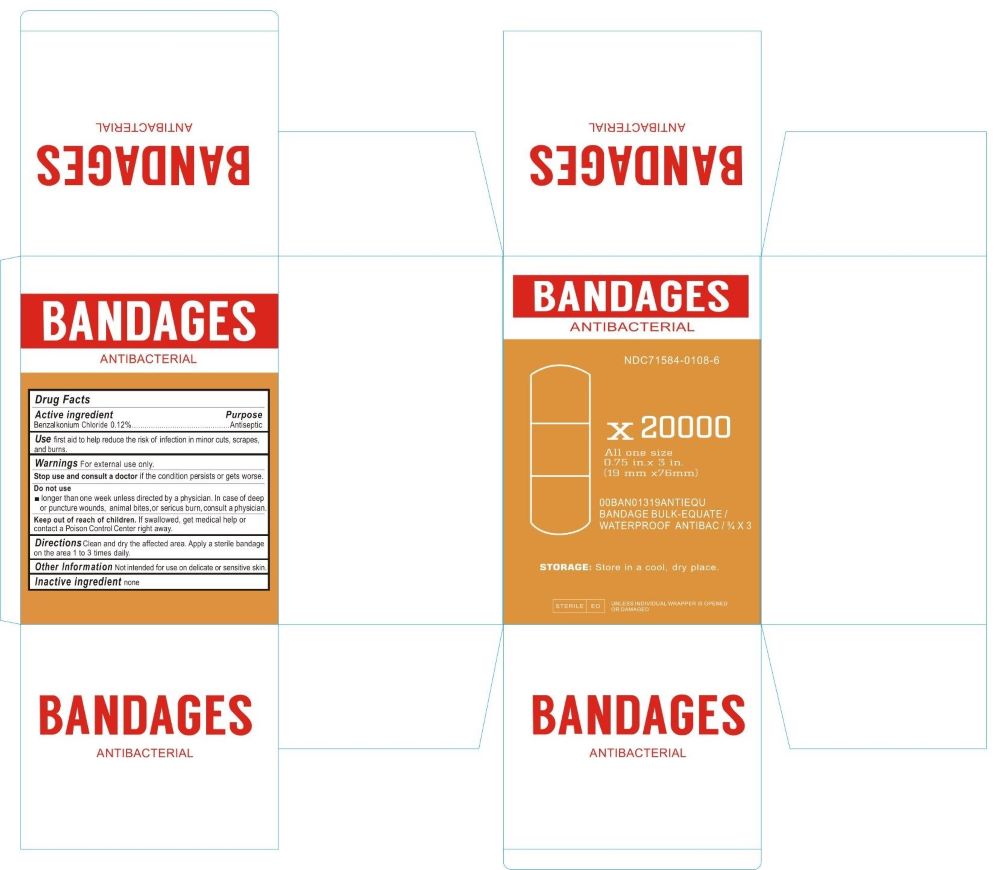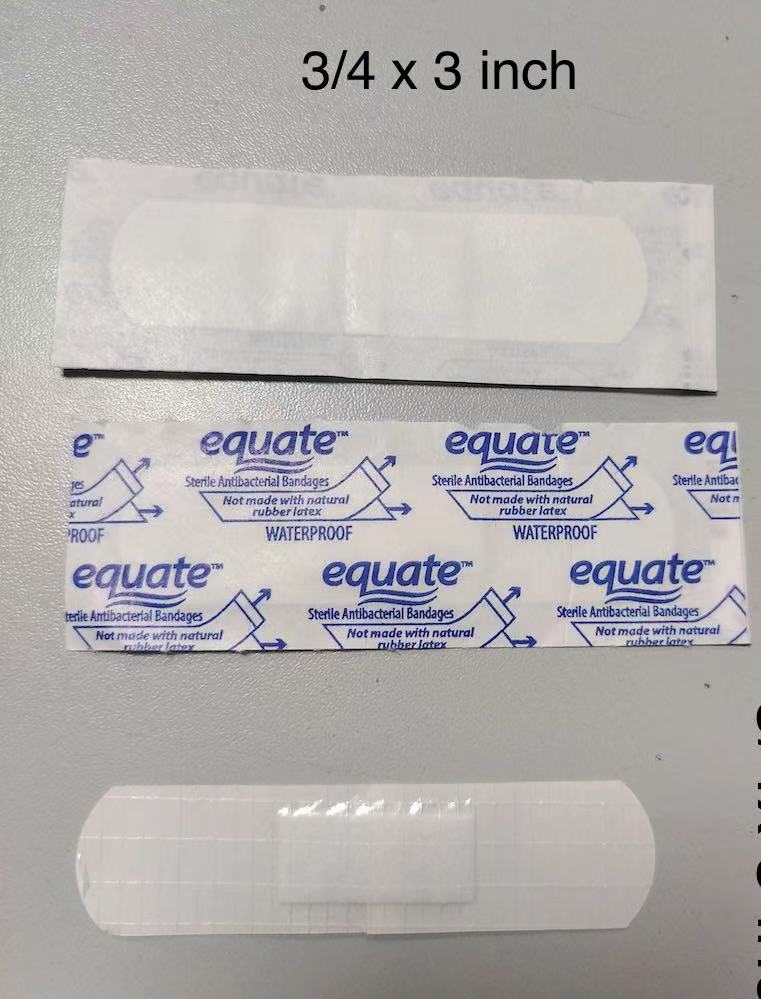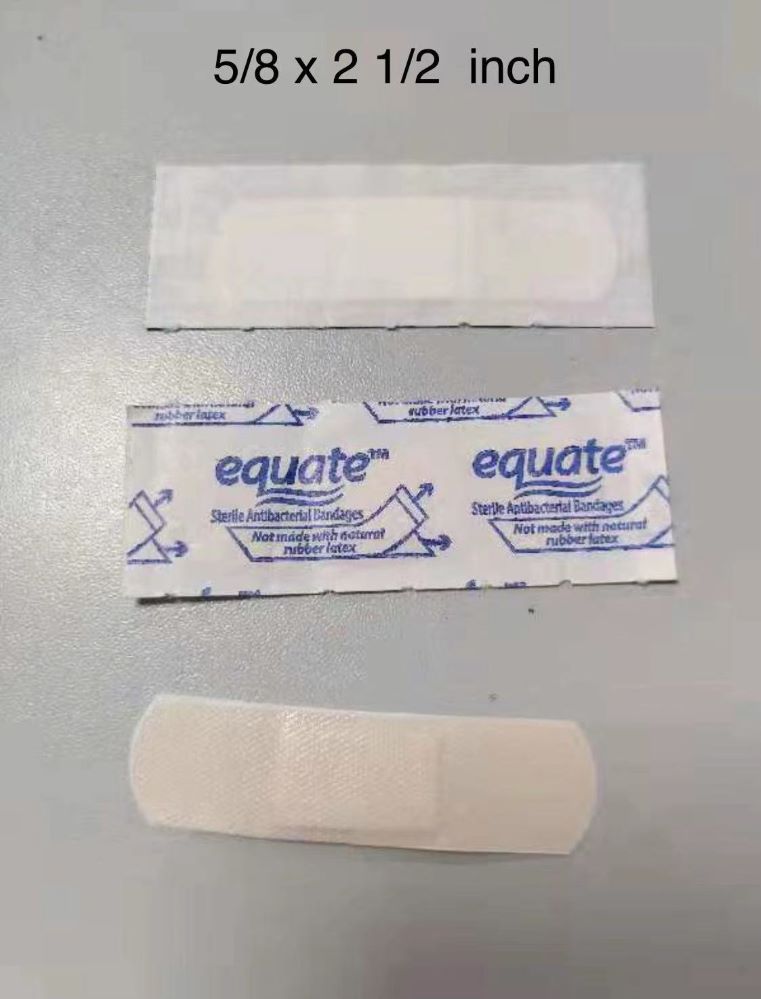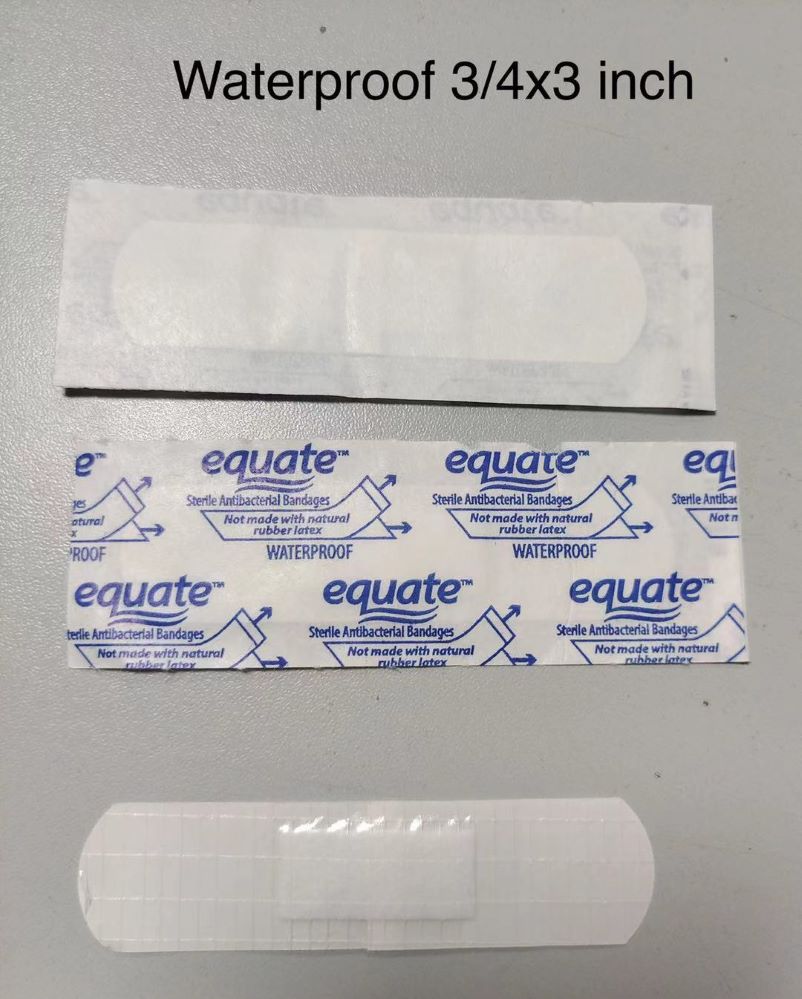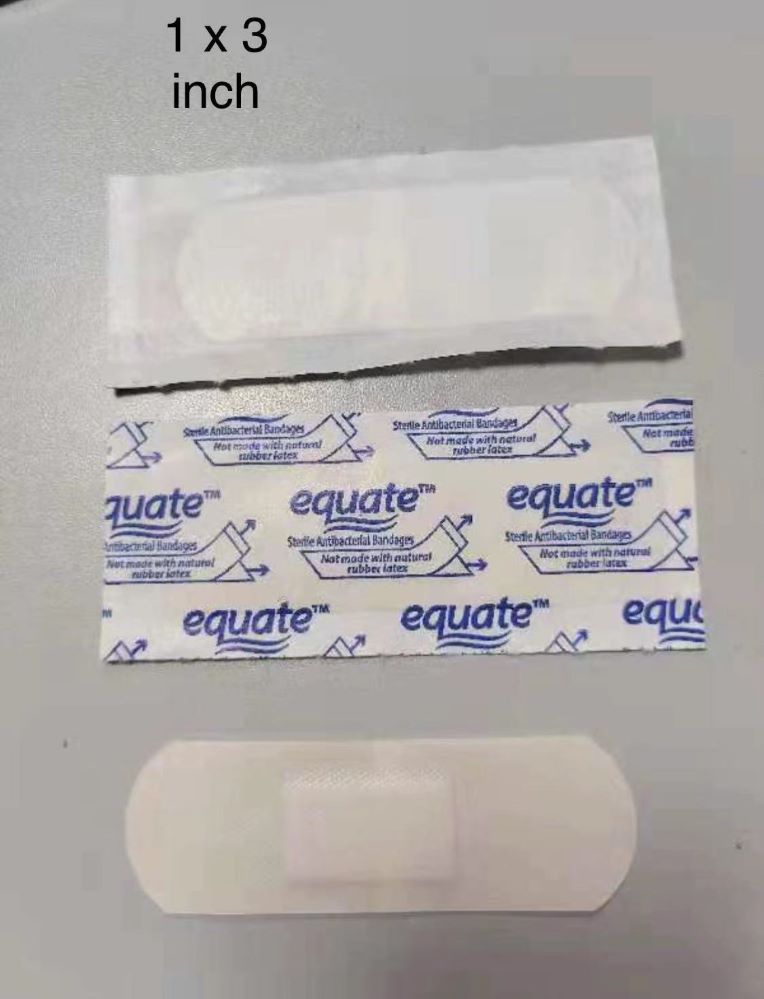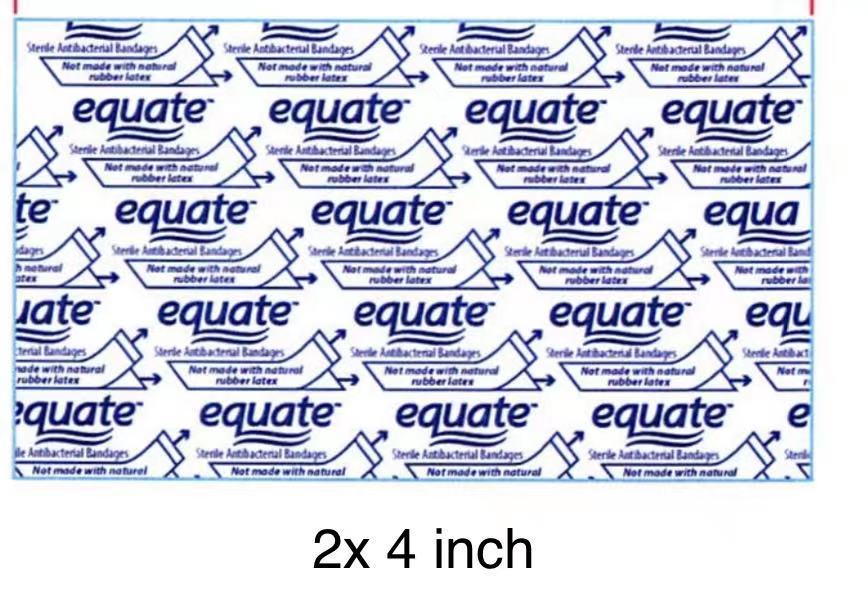 DRUG LABEL: ANTIBACTERIAL BANDAGES
NDC: 71584-0108 | Form: DRESSING
Manufacturer: Guangdong Comfort Medical Products Co., Ltd.
Category: otc | Type: HUMAN OTC DRUG LABEL
Date: 20251019

ACTIVE INGREDIENTS: BENZALKONIUM CHLORIDE 0.12 g/100 g
INACTIVE INGREDIENTS: COTTON FIBER

ANTIBACTERIAL BANDAGES

ACTIVE INGREDIENTS

Benzalkonium Chloride 0.12%

Purpose

Antiseptic

USE

First aid to help reduce the risk of infection in minor cuts, scrapes, and burns.

WARNINGS

For external use only.

Stop use and consult a doctor if the condition persists or gets worse.

Do not use longer than 1 week unless directed by a physician. In case of deep or puncture wounds, animal bites, or serious burn, consult a physician.

Keep out of reach of children. if swallowed get medical help or contact Poison control Center right away.

DIRECTIONS

Clean and dry the affected area. Apply a sterile bandage on the area 1 to 3 times daily.

Other Information

Not intended for use on delicate or sensitive skin.

INACTIVE INGREDIENT

None

Keep out of reach of children. if swallowed get medical help or contact Poison control Center right away.

Dosage and administration

Apply a sterile bandage on the affected area 1 to 3 times daily.

Label principal display panel

NDC 71584-0108-1

ANTIBACTERIAL BANDAGES

Drug Facts

ACTIVE INGREDIENTS
Benzalkonium Chloride 0.12%

Purpose
Antiseptic

USE
First aid to help reduce the risk of infection in minor cuts, scrapes, and burns.

WARNINGS For external use only.

Stop use and consult a doctor if the condition persists or gets worse.

Do not use
longer than one week unless directed by a physician. In case of deep or puncture wounds, animal bites, or serious burn, consult a physician.

Keep out of reach of children. if swallowed get medical help or contact Poison control Center right away.

DIRECTIONS
Clean and dry the affected area. Apply a sterile bandage on the area 1 to 3 times daily.

Other Information: not intended for use on delicate or sensitive skin.

INACTIVE INGREDIENT